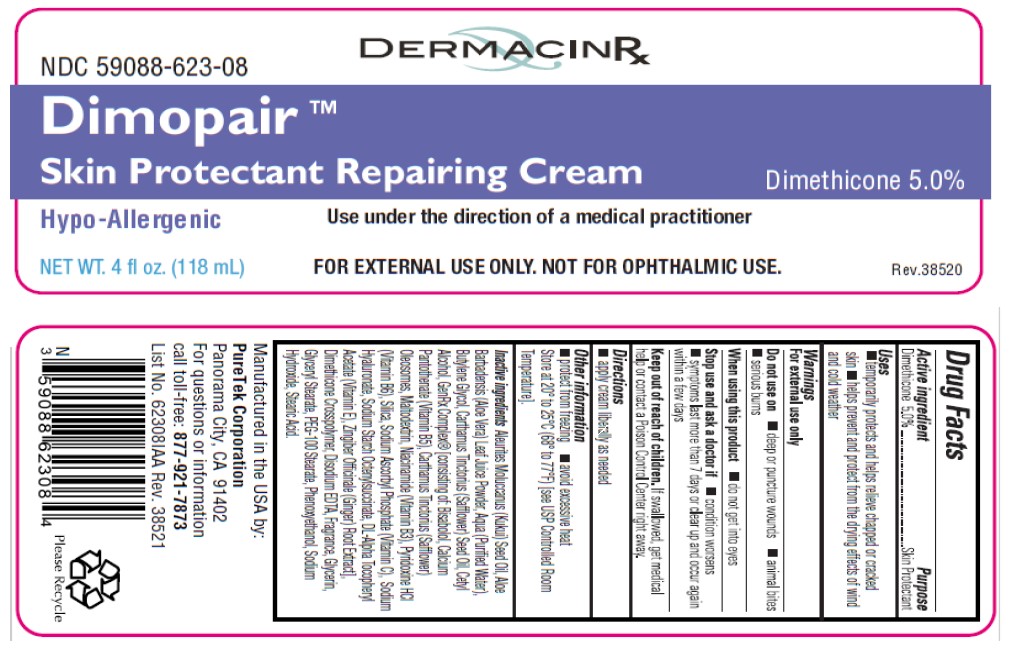 DRUG LABEL: Dimopair
NDC: 59088-623 | Form: CREAM
Manufacturer: PureTek Corporation
Category: otc | Type: HUMAN OTC DRUG LABEL
Date: 20241001

ACTIVE INGREDIENTS: DIMETHICONE 50 mg/1 mL
INACTIVE INGREDIENTS: DIMETHICONE/DIENE DIMETHICONE CROSSPOLYMER; KUKUI NUT OIL; ALOE VERA LEAF; BUTYLENE GLYCOL; SAFFLOWER OIL; CETYL ALCOHOL; GLYCERIN; GLYCERYL MONOSTEARATE; LEVOMENOL; CALCIUM PANTOTHENATE; CARTHAMUS TINCTORIUS SEED OLEOSOMES; MALTODEXTRIN; NIACINAMIDE; PYRIDOXINE HYDROCHLORIDE; SILICON DIOXIDE; SODIUM ASCORBYL PHOSPHATE; .ALPHA.-TOCOPHEROL ACETATE, DL-; GINGER; PEG-100 STEARATE; PHENOXYETHANOL; WATER; HYALURONATE SODIUM; STEARIC ACID; SODIUM HYDROXIDE; EDETATE DISODIUM ANHYDROUS; ALUMINUM STARCH OCTENYLSUCCINATE

Dimopair

Active ingredient

Dimethicone 5.0%

Purpose

Skin Protectant

Uses

■ temporarily protects and helps relieve chapped or cracked skin

■ helps prevent and protect from the drying effects of wind and cold weather

Warnings

For external use only

Do not use on

■ deep or puncture wounds ■ animal bites ■ serious burns

When using this product

■ do not get into eyes

Stop use and ask a doctor if

■ condition worsens
■ symptoms last more than 7 days or clear up and occur again within a few days

Keep out of reach of children.

If swallowed, get medical help or contact a Poison Control Center right away.

Directions

■ apply cream liberally as needed

Other information

■ protect from freezing ■ avoid excessive heat

Store at 20° to 25°C (68° to 77°F) [see USP Controlled Room Temperature].

Inactive ingredients

Aleuritis Moluccanus (Kukui) Seed Oil, Aloe Barbadensis (Aloe Vera) Leaf Juice Powder, Aqua (Purified Water), Butylene Glycol, Carthamus Tinctorius (Safflower) Seed Oil, Cetyl Alcohol, GenRx Complex® [consisting of: Bisabolol, Calcium Pantothenate (Vitamin B5), Carthamus Tinctorius (Safflower) Oleosomes, Maltodextrin, Niacinamide (Vitamin B3), Pyridoxine HCl (Vitamin B6), Silica, Sodium Ascorbyl Phosphate (Vitamin C), Sodium Hyaluronate, Sodium Starch Octenylsuccinate, DL-Alpha Tocopheryl Acetate (Vitamin E), Zingiber Officinale (Ginger) Root Extract], Dimethicone Crosspolymer, Disodium EDTA, Fragrance, Glycerin, Glyceryl Stearate, PEG-100 Stearate, Phenoxyethanol, Sodium Hydroxide, Stearic Acid.

Dimopair™

Manufactured in the USA by:
PureTek Corporation
Panorama City, CA 91402
For questions or information
call toll-free: 877-921-7873